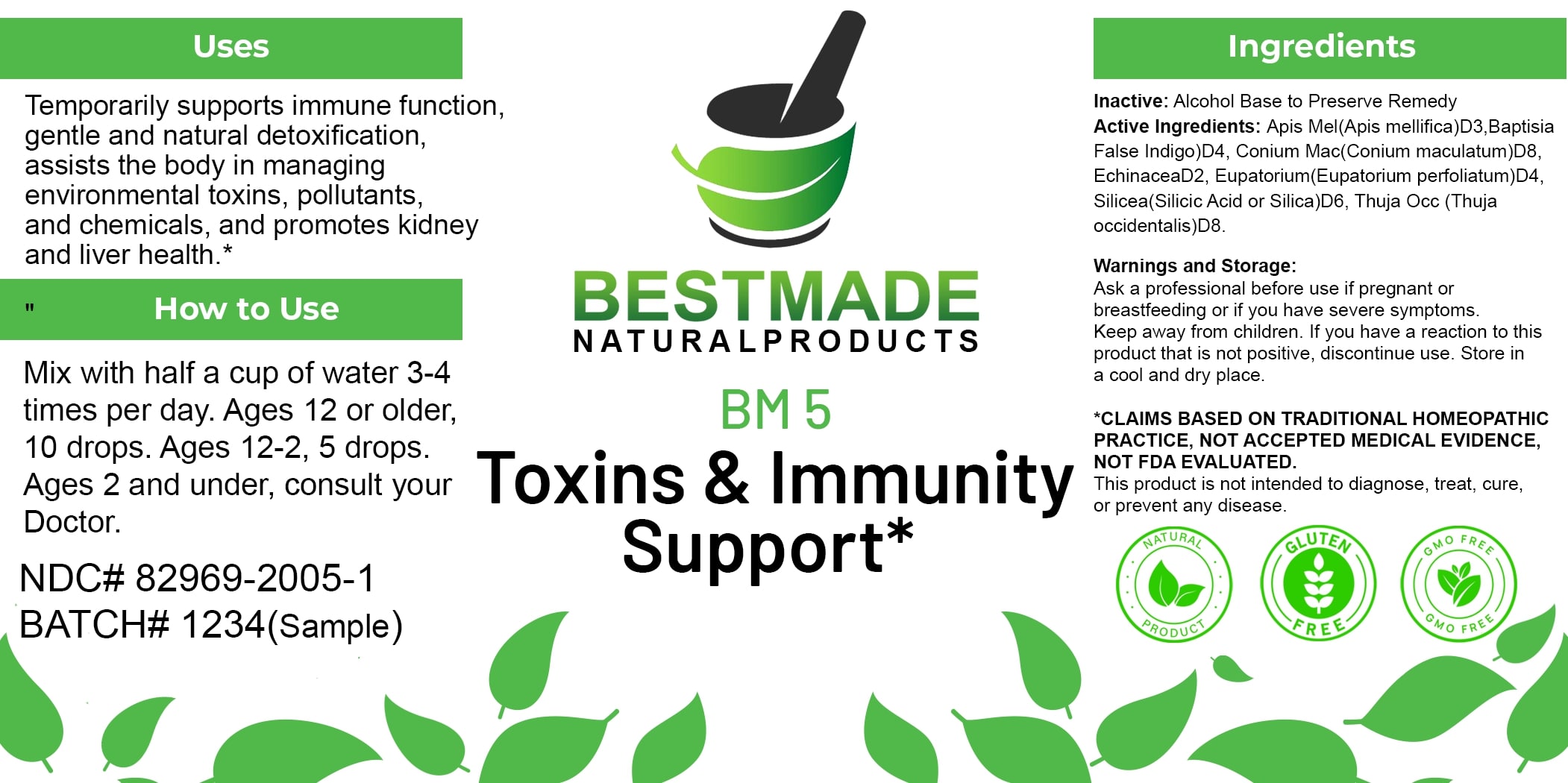 DRUG LABEL: Bestmade Natural Products BM5
NDC: 82969-2005 | Form: LIQUID
Manufacturer: Bestmade Natural Products
Category: homeopathic | Type: HUMAN OTC DRUG LABEL
Date: 20250122

ACTIVE INGREDIENTS: THUJA OCCIDENTALIS LEAF 30 [hp_C]/30 [hp_C]; ECHINACEA ANGUSTIFOLIA 30 [hp_C]/30 [hp_C]; BAPTISIA TINCTORIA ROOT 30 [hp_C]/30 [hp_C]; EUPATORIUM PERFOLIATUM FLOWERING TOP 30 [hp_C]/30 [hp_C]; SILICON DIOXIDE 30 [hp_C]/30 [hp_C]; APIS MELLIFERA 30 [hp_C]/30 [hp_C]; CONIUM MACULATUM FLOWERING TOP 30 [hp_C]/30 [hp_C]
INACTIVE INGREDIENTS: ALCOHOL 30 [hp_C]/30 [hp_C]

BM5

DOSAGE AND ADMINISTRATION

How to Use

Mix with half a cup of water 3-4 times per day. Ages 12 or older, 10 drops. Ages 12-2, 5 drops. Ages 2 and under, consult your Doctor.

Inactive:

Alcohol Base to Preserve Product

INDICATIONS AND USAGE

Temporarily supports immune function, gentle and natural detoxification, assists the body in managing environmental toxins, pollutants, and chemicals, and promotes kidney and liver health.*

*Claims Based on Traditional Homeopathic Practice, Not Accepted Medical Evidence, Not FDA Evaluated.

This product is not intended to diagnose, treat, cure, or prevent any disease.

Active Ingredients:

Apis Mel (Apis mellifica)D3, Baptisia False Indigo)D4, Conium Mac (Conium maculatum)D8, EchinaceaD2, Eupatorium (Eupatorium perfoliatum)D4, Silicea (Silicic Acid or Silica)D6, Thuja Occ (Thuja occidentalis)D8.

KEEP OUT OF REACH OF CHILDREN

Warnings and Storage:

Ask a professional before use if pregnant or breastfeeding or if you have severe symptoms. Keep away from children. If you have a reaction to this product that is not positive, discontinue use. Store in a cool and dry place.

PURPOSE

Temporarily supports immune function, gentle and natural detoxification, assists the body in managing environmental toxins, pollutants, and chemicals, and promotes kidney and liver health.*

*Claims Based on Traditional Homeopathic Practice, Not Accepted Medical Evidence, Not FDA Evaluated.

This product is not intended to diagnose, treat, cure, or prevent any disease.

Warnings and Storage:

Ask a professional before use if pregnant or breastfeeding or if you have severe symptoms. Keep away from children. If you have a reaction to this product that is not positive, discontinue use. Store in a cool and dry place.

Claims Based on Traditional Homeopathic Practice, Not Accepted Medical Evidence, Not FDA Evaluated.

This product is not intended to diagnose, treat, cure, or prevent any disease.

Entire package label